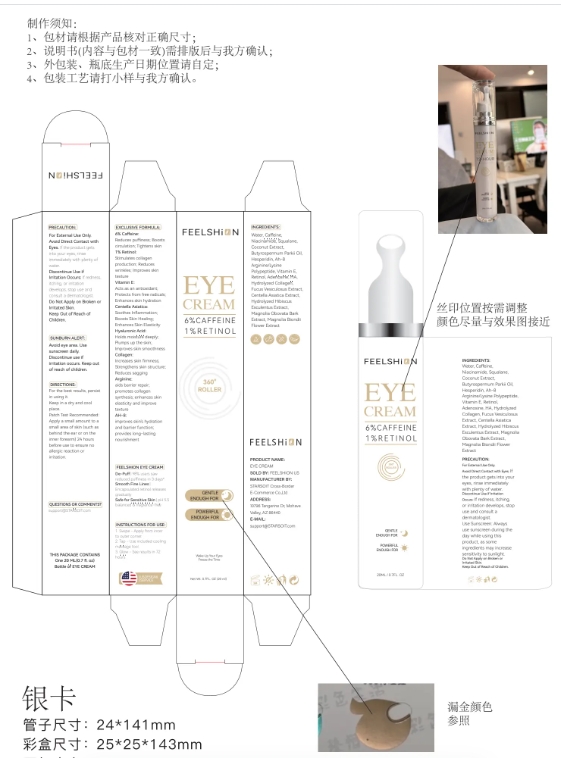 DRUG LABEL: FEELSHION 6% Caffeine 1% Retinol Eye Cream
NDC: 85212-0021 | Form: CREAM
Manufacturer: Beijing JUNGE Technology Co., Ltd.
Category: otc | Type: HUMAN OTC DRUG LABEL
Date: 20250303

ACTIVE INGREDIENTS: CAFFEINE 6 g/100 mL
INACTIVE INGREDIENTS: ADENOSINE 1 mL/100 mL; FUCUS VESICULOSUS 0.2 mL/100 mL; HIBISCUS ESCULENTUS SEED EXTRACT 0.1 mL/100 mL; MAGNOLIA OBOVATA BARK 0.1 mL/100 mL; MAGNOLIA BIONDII FLOWER 0.1 mL/100 mL; ARGININE 1 mL/100 mL; WATER 77.3 mL/100 mL; NIACINAMIDE 3 mL/100 mL; HESPERIDIN 2 mL/100 mL; SQUALANE 3 mL/100 mL; CENTELLA ASIATICA 0.2 mL/100 mL; TOCOPHEROL 1 mL/100 mL; SODIUM HYALURONATE 0.5 mL/100 mL; HYDROLYZED PORCINE COLLAGEN (ENZYMATIC; 3000 MW) 0.5 mL/100 mL; BUTYROSPERMUM PARKII (SHEA) BUTTER 2 mL/100 mL; COCOS NUCIFERA (COCONUT) FRUIT 2 mL/100 mL

PRECAUTIONS

For External Use Only.

Avoid Direct Contact with Eyes.

lf the product getsinto your eyes, rinseimmediately with plenty of Water.
Discontinue Use iflrritation Occurs: lf redness itching, or irritation develops.stop use andconsult a dermatologist

Do Not Apply on Broken or lrritated Skin.Keep Out of Reach of Children.

WARNINGS

Avoid cye area. Use sunscreen daily.Discontinue use ifirritation occurs, Keep out of reach of children.

INSTRUCTIONS FOR USE

Swipe - Apply from inner to outer corner.

Tap -Use included cooling massage tool.

Glow-See results in 72 hours.

DOSAGE AND ADMINISTRATION

Net WE 0.7FL. OZ (20 mI)

INACTIVE INGREDIENT

WATER
NIACINAMIDE
SQUALANE
COCOS NUCIFERA (COCONUT) FRUIT EXTRACT
BUTYROSPERMUM PARKII (SHEA BUTTER) OIL
HESPERIDIN
ARGININE/LYSINE POLYPEPTIDE
TOCOPHEROL
ADENOSINE
SODIUM HYALURONATE
HYDROLYZED COLLAGEN
FUCUS VESICULOSUS EXTRACT
CENTELLA ASIATICA EXTRACT
HYDROLYZED HIBISCUS ESCULENTUS EXTRACT
MAGNOLIA OBOVATA BARK EXTRACT
MAGNOLIA BIONDII FLOWER EXTRACT

INDICATIONS AND USAGE

De-Puff |98% users saw reduced puffiness in 3 days*

Smooth Fine Lines | Encapsulated retinol releases gradually

Safe for Sensitive Skin | pH 5.5balanced

balanceced&fragrance-free

KEEP OUT OF REACH OF CHILDREN

In case of accidental ingestion, seek medical advice immediately orcontact a Poison Control Center right away.

PURPOSE

Reduces puffiness;
Reduces wrinkdies;

Improves skin texture;

Enhances skin hydration